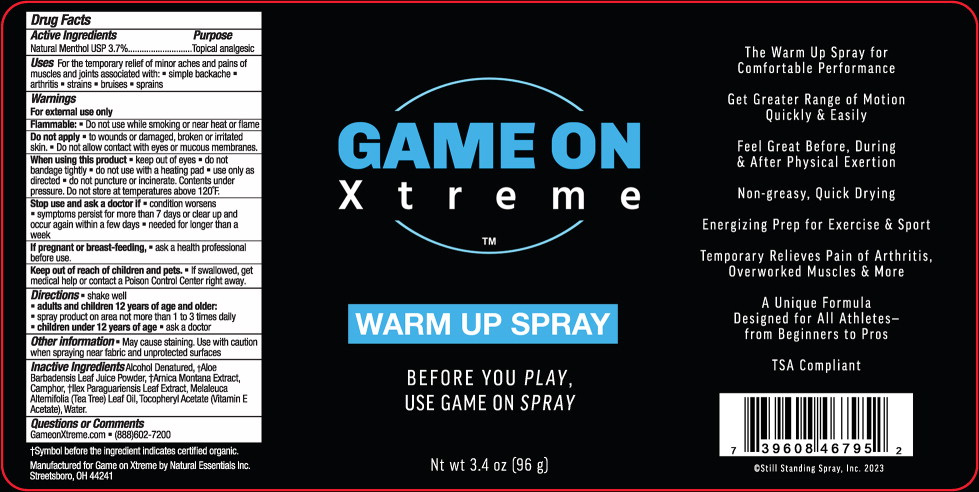 DRUG LABEL: Game On Xtreme
NDC: 66902-166 | Form: LIQUID
Manufacturer: Natural Essentials Inc.
Category: otc | Type: HUMAN OTC DRUG LABEL
Date: 20250723

ACTIVE INGREDIENTS: MENTHOL, UNSPECIFIED FORM 37 mg/1 g
INACTIVE INGREDIENTS: ALCOHOL; ALOE VERA LEAF; ARNICA MONTANA FLOWER; CAMPHOR (SYNTHETIC); .ALPHA.-TOCOPHEROL ACETATE; ILEX PARAGUARIENSIS LEAF; TEA TREE OIL; WATER

Drug Facts

Active Ingredients

Natural Menthol USP 3.7%

Purpose

Topical analgesic

Uses

For the temporary relief of minor aches and pains of muscles and joints associated with:

- simple backache
- arthritis
- strains
- bruises
- sprains

Warnings

For external use only

Flammable:

- Do not use while smoking or near heat or flame

Do not apply

- to wounds or damaged, broken or irritated skin.
- Do not allow contact with eyes or mucous membranes.

When using this product

- keep out of eyes
- do not bandage tightly
- do not use with a heating pad
- use only as directed
- do not puncture or incinerate. Contents under pressure. Do not store at temperatures above 120°F.

Stop use and ask a doctor if

- condition worsens
- symptoms persist for more than 7 days or clear up and occur again within a few days
- needed for longer than a week

If pregnant or breast-feeding,

- ask a health professional before use.

Keep out of reach of children and pets.

- If swallowed, get medical help or contact a Poison Control Center right away.

Directions

- shake well
- adults and children 12 years of age and older:
- spray product on area not more than 1 to 3 times daily
- children under 12 years of age
- ask a doctor

Other information

May cause staining. Use with caution when spraying near fabric and unprotected surfaces

Inactive Ingredients

Alcohol Denatured, †Aloe Barbadensis Leaf Juice Powder, †Arnica Montana Extract, Camphor, †Ilex Paraguariensis Leaf Extract, Melaleuca Altemifolia (Tea Tree) Leaf Oil, Tocopheryl Acetate (Vitamin E Acetate), Water.

Questions or Comments

GameonXtreme.com ■ (888)602-7200

†Symbol before the ingredients indicates certified organic.

Principal Display Panel – 96g Can Label

GAME ON

Xtreme™

WARM UP SPRAY

BEFORE YOU PLAY,

USE GAME ON SPRAY

Nt wt 3.4 oz (96 g)